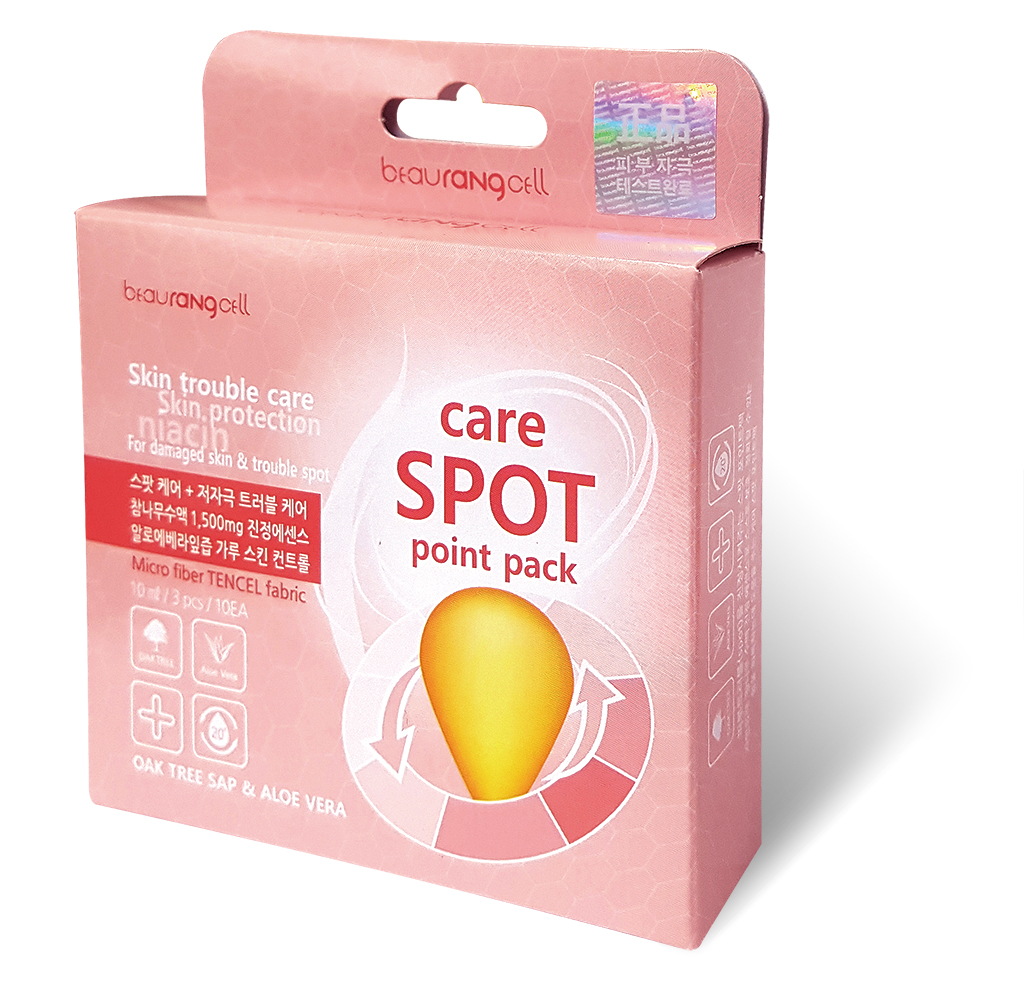 DRUG LABEL: Beaurangcell
NDC: 71962-0001 | Form: PATCH
Manufacturer: Modoo plan
Category: otc | Type: HUMAN OTC DRUG LABEL
Date: 20180108

ACTIVE INGREDIENTS: QUERCUS ACUTISSIMA WHOLE 10 g/100 mL
INACTIVE INGREDIENTS: ALOE VERA LEAF

ACTIVE INGREDIENT

Quercus Acutissima Sap

INACTIVE INGREDIENT

Aloe Barbadensis Leaf Juice Powder

PURPOSE

Skin protection, Skin trouble care

keep out or reach of the children

INDICATIONS AND USAGE

1) Apply toner to face

2) Apply patch to the desired area

3) After 15-20 min, wipe remove patch and pat the remaining essence.

WARNINGS

1) Discontinue use or consult dermatologist if irritation, itching or swelling appears after applying the product.

2) Avoid applying patches on the wounded, inflamed or other uncomfortable skin part.

3) Cautions for the storage and handling a) Keep out of children. B) Avoid hot or cold and direct sunlight. c) After unpacking, use the patches immediately to prevent deterioration.

DOSAGE AND ADMINISTRATION

for external use only